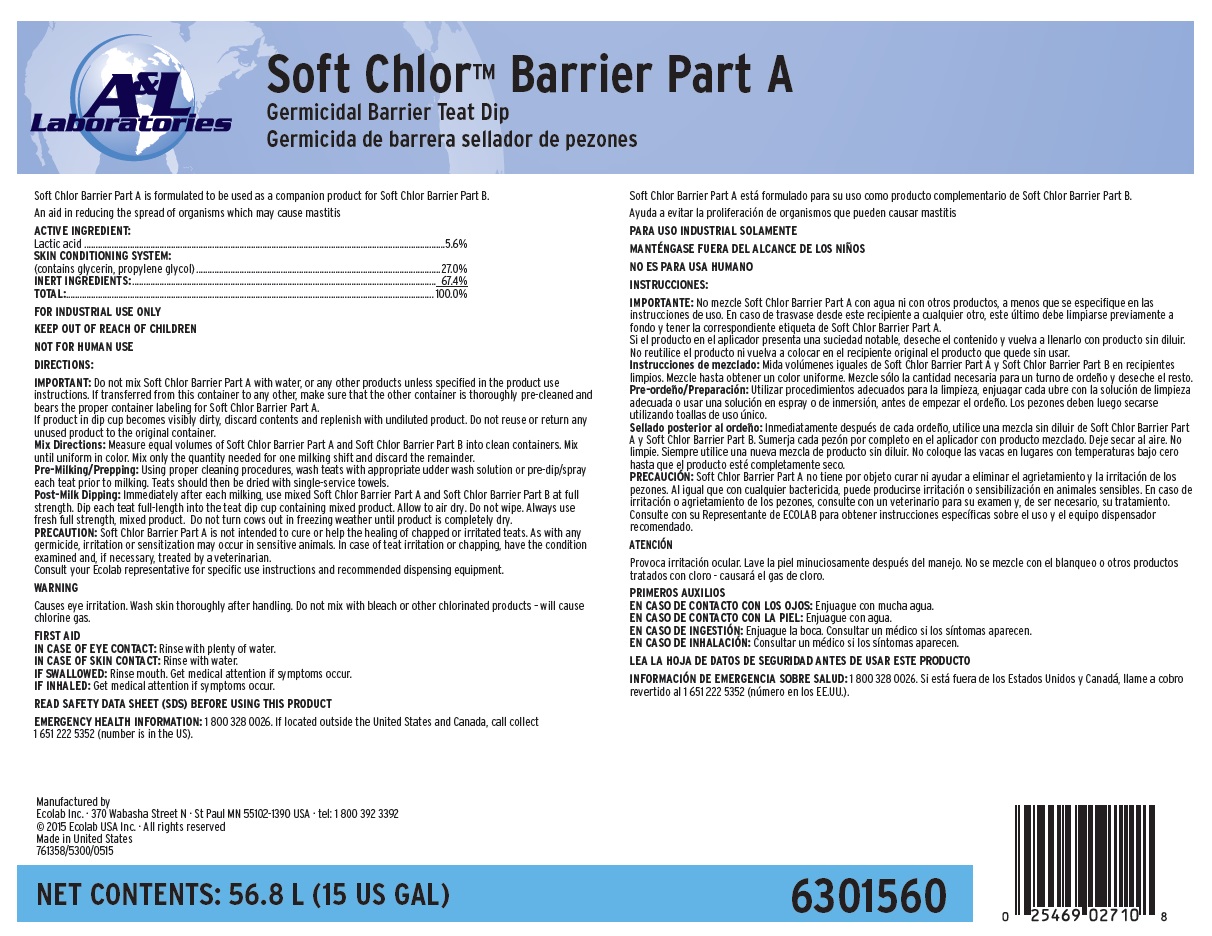 DRUG LABEL: Soft Chlor Barrier Part A
NDC: 47593-569 | Form: SOLUTION
Manufacturer: Ecolab Inc.
Category: animal | Type: OTC ANIMAL DRUG LABEL
Date: 20251011

ACTIVE INGREDIENTS: LACTIC ACID 56 mg/1 mL
INACTIVE INGREDIENTS: WATER; GLYCERIN; PROPYLENE GLYCOL

SAFE HANDLING WARNING

FOR INDUSTRIAL USE ONLY

KEEP OUT OF REACH OF CHILDREN

NOT FOR HUMAN USE

DIRECTIONS:

IMPORTANT: Do not mix Soft Chlor Barrier Part A with water, or any other products unless specified in the product use
instructions. If transferred from this container to any other, make sure that the other container is thoroughly pre-cleaned and
bears the proper container labeling for Soft Chlor Barrier Part A.
If product in dip cup becomes visibly dirty, discard contents and replenish with undiluted product. Do not reuse or return any
unused product to the original container.
Mix Directions: Measure equal volumes of Soft Chlor Barrier Part A and Soft Chlor Barrier Part B into clean containers. Mix
until uniform in color. Mix only the quantity needed for one milking shift and discard the remainder.
Pre-Milking/Prepping: Using proper cleaning procedures, wash teats with appropriate udder wash solution or pre-dip/spray
each teat prior to milking. Teats should then be dried with single-service towels.
Post-Milk Dipping: Immediately after each milking, use mixed Soft Chlor Barrier Part A and Soft Chlor Barrier Part B at full
strength. Dip each teat full-length into the teat dip cup containing mixed product. Allow to air dry. Do not wipe. Always use
fresh full strength, mixed product. Do not turn cows out in freezing weather until product is completely dry.
PRECAUTION: Soft Chlor Barrier Part A is not intended to cure or help the healing of chapped or irritated teats. As with any
germicide, irritation or sensitization may occur in sensitive animals. In case of teat irritation or chapping, have the condition
examined and, if necessary, treated by a veterinarian.
Consult your Ecolab representative for specific use instructions and recommended dispensing equipment.

WARNING

Causes eye irritation. Wash skin thoroughly after handling. Do not mix with bleach or other chlorinated products – will cause
chlorine gas.

FIRST AID
IN CASE OF EYE CONTACT: Rinse with plenty of water.
IN CASE OF SKIN CONTACT: Rinse with water.
IF SWALLOWED: Rinse mouth. Get medical attention if symptoms occur.
IF INHALED: Get medical attention if symptoms occur

READ SAFETY DATA SHEET (SDS) BEFORE USING THIS PRODUCT

EMERGENCY HEALTH INFORMATION: 1 800 328 0026. If located outside the United States and Canada, call collect
1 651 222 5352 (number is in the US).

PACKAGE LABEL

A&L Laboratories

Soft Chlor™ Barrier Part A

Germicidal Barrier Teat Dip

Germicida de barrera sellador de pezones

Manufactured by
Ecolab Inc. · 370 Wabasha Street N · St Paul MN 55102-1390 USA · tel: 1 800 392 3392
© 2015 Ecolab USA Inc. · All rights reserved
Made in United States

761358/5300/0515

NET CONTENTS: 56.8 L (15 US GAL)

6301560